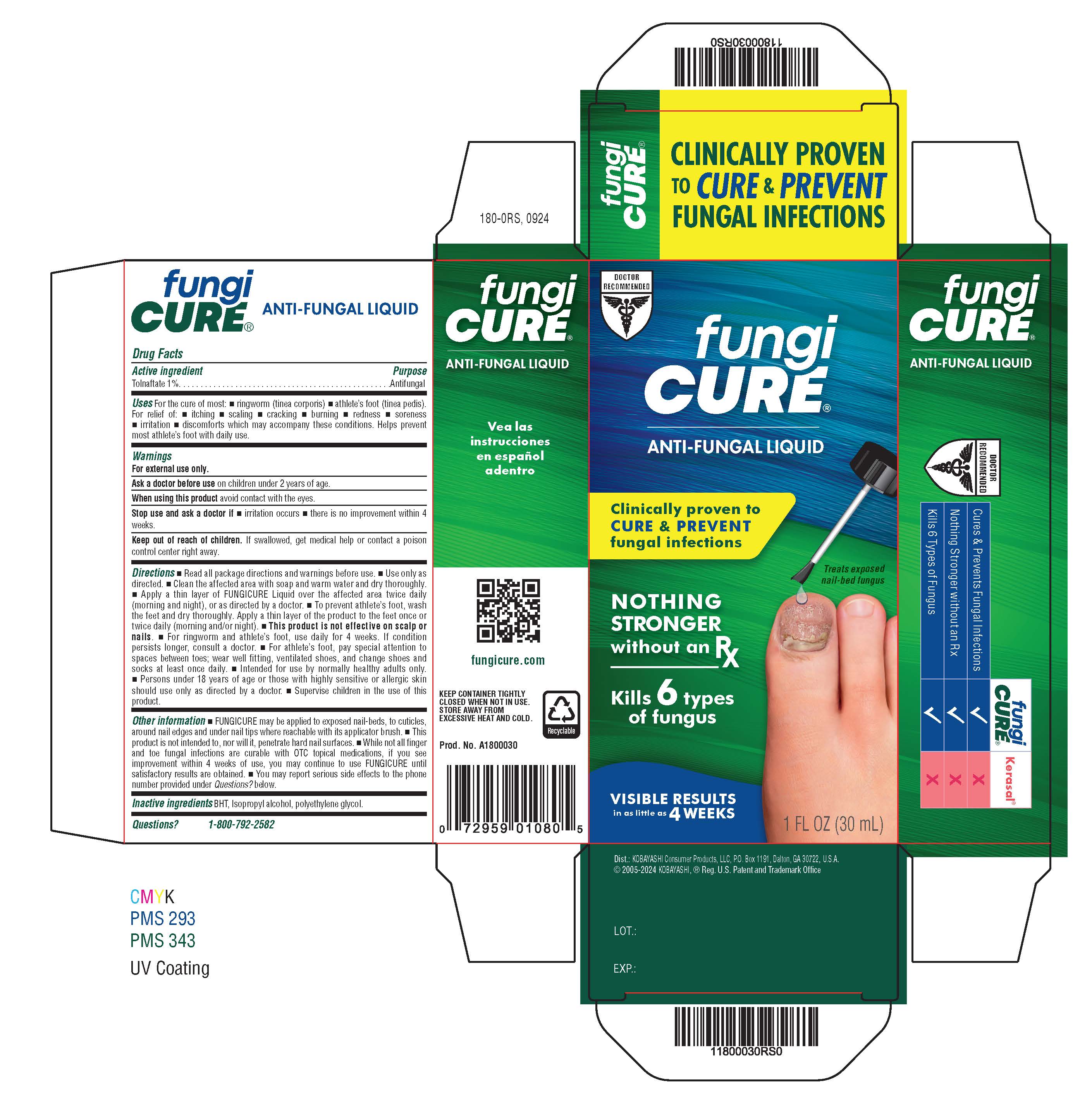 DRUG LABEL: Fungicure Anti-Fungal Liquid
NDC: 52389-298 | Form: LIQUID
Manufacturer: Kobayashi Healthcare International, Inc.
Category: otc | Type: HUMAN OTC DRUG LABEL
Date: 20250922

ACTIVE INGREDIENTS: TOLNAFTATE 8.65 mg/1 mL
INACTIVE INGREDIENTS: POLYETHYLENE GLYCOL 400; ISOPROPYL ALCOHOL; BUTYLATED HYDROXYTOLUENE

Fungicure Anti-Fungal Liquid (tolnaftate)

Active ingredient

Tolnaftate 1%

Purpose

Antifungal

Uses

For the cure of most:

- ringworm (tinea corporis)
- athlete's foot (tinea pedis)

For relief of:

- itching
- scaling
- cracking
- burning
- redness
- soreness
- irritation
- discomforts which may accompany these conditions

Helps prevent most athlete's foot with daily use.

Warnings

For external use only

Ask a doctor before use

on children under 2 years of age

When using this product

avoid contact with the eyes.

Stop use and ask a doctor if

- irritation occurs
- there is no improvement within 4 weeks

Keep out of reach of children.

If swallowed, get medical help or contact a poison control center right away.

Directions

- Read all package directions and warnings before use.
- Use only as directed.
- Clean the affected area with soap and warm water and dry thoroughly.
- Apply a thin layer of FUNGICURE Liquid over the affected area twice daily (morning and night), or as directed by a doctor.
- To prevent athlete's foot, wash the feet and dry thoroughly. Apply a thin layer of the product to the feet once or twice daily (morning and/or night).
- This product is not effective on scalp or nails.
- For ringworm and athlete's foot, use daily for 4 weeks. If condition persists longer, consult a doctor.
- For athlete's foot, pay special attention to spaces between toes; wear well fitting, ventillated shoes, and change shoes and socks at least once daily.
- Intended for use for use by normally healthy adults only.
- Persons under 18 years of age or those with highly sensitive or allergic skin should use only as directed by a doctor.
- Supervise children in the use of this product.

Other Information

- FUNGICURE may be applied to exposed nail-beds, to cuticles, around nail edges and under nail tips where reachable with its applicator brush.
- This product is not intended to, nor will it, penetrate hard nail surfaces.
- While not all finger and toe fungal infections are curable with OTC topical medication, if you see improvement within 4 weeks of use, you may continue to use FUNGICURE until satisfactory results are obtained
- You may report serious side effects to the phone number provided under Questions? below.

Inactive ingredients

BHT, Isopropyl alcohol, Polyethylene glycol

Questions?

1-800-792-2582 www.fungicure.com

Insert Text

Fungicure

ANTI-FUNGAL LIQUID

THE FINGER & TOE FUNGI SPECIALIST

NOTHING STRONGER without an Rx

Visible Results in as Little as 4 Weeks

Kills 6 Types of Fungus

WHAT IS FUNGUS INFECTION OF THE FINGER AND TOES? Common topical fungus infections of the finger and toes are caused by a variety of fungi; actual living organisms (members of the yeast and mold family) which thrive in dark, moist conditions. Using small breaches in the skin’s surface, these organisms can cause infection by contact with infected surfaces, animals, or people. Once infection starts, spreading may occur. For example, infected fingers and toes may infect other fingers and toes. Although such infections often develop slowly, they may be difficult to eliminate if not treated promptly with an effective anti-fungal medicine like FUNGICURE.

HOW DO YOU KNOW IF YOU HAVE A TOPICAL FUNGUS INFECTION? Some topical fungal infections may present themselves on the skin surface as ring-like formations with clear centers; this is commonly called ringworm. Athlete’s foot fungus, when in the finger and toe areas, is often characterized by scaling of skin, burning, cracking, itching, and related discomforts. When nails become infected, they may appear to become opaque (cloudy white), thickened, brittle, easily broken, and in some cases, discolored (greenish/brown).

UNDERSTANDING AND TREATING A NAIL AREA INFECTION: Fungal infections of the nail areas are often caused by the same fungi that lead to athlete’s foot and ringworm infections elsewhere on the body. These fungi can infect the entire area around the nails including the cuticles, the nail beds, and even the nails themselves. When infected finger/toe nails are intact, over-the-counter topical anti-fungal treatments may not be able to penetrate the nail and kill the fungus; this is why all OTC topical treatments must indicate they are not effective on the nails. However, in instances of advanced infection, the nails often are not intact; they may be missing, cracked open, or lifted away, exposing the infected nail bed. In these instances FUNGICURE Anti-Fungal Liquid, with its powerful anti-fungal formula, can reach and kill nail bed fungus by direct application or related capillary action. FUNGICURE cures the infection, allowing the natural regrowth of healthy looking tissue.

NOTE: Fungal infections which are isolated beneath an intact nail or embedded within the nail itself may require consultation from a doctor for proper treatment.

HOW FUNGICURE LIQUID WORKS:

MAXIMUM STRENGTH FUNGICURE Liquid contains tolnaftate, a widely recognized anti-fungal ingredient that has been proven to be effective against 6 types of fungi such as E. floccosum, T. mentagrophytes, M. canis, M. gypseum, T. tonsurans and T. rubrum.

When applied as directed, FUNGICURE Liquid acts promptly to target, destroy, and prevent the spread of infection by inhibiting the growth and reproduction of fungal cells.

PROMPT ACTION AND PROPER TREATMENT:

Early treatment of fungal infections is important. If you suspect that you may have a fungal infection, consult your doctor promptly for advice and proper diagnosis. You may wish to show him/her FUNGICURE Liquid and discuss its use. For best results, once treatment is started with FUNGICURE Liquid, it is important to carefully follow the treatment instructions on the package until satisfactory results are achieved or advised further by a doctor.

NOTE: Noticeable improvement may be expected within 4 weeks in the case of most ringworm and athlete's foot fungus. Consult your doctor for advice if noticeable improvement is not evident by this time or if the condition persists or worsens.

Active ingredient: Tolnaftate 1%

Uses: For the cure of most: • ringworm (tinea corporis) • athlete’s foot (tinea pedis). For relief of: • itching • scaling • cracking • burning • redness • soreness • irritation • discomforts which may accompany these conditions. Helps prevent most athlete’s foot with daily use.

Warnings:

For external use only.

Ask a doctor before use on children under 2 years of age.

When using this product avoid contact with the eyes.

Stop use and ask a doctor if • irritation occurs • there is no improvement within 4 weeks.

Keep out of reach of children. If swallowed, get medical help or contact a poison control center right away.

Directions: • Read all package directions and warnings before use. • Use only as directed. • Clean the affected area with soap and warm water and dry thoroughly. • Apply a thin layer of FUNGICURE Liquid over the affected area twice daily (morning and night), or as directed by a doctor. • To prevent athlete's foot, wash the feet and dry thoroughly. Apply a thin layer of the product to the feet once or twice daily (morning and/or night). • This product is not effective on scalp or nails. • For ringworm and athlete’s foot, use daily for 4 weeks. If condition persists longer, consult a doctor. • For athlete’s foot, pay special attention to spaces between toes; wear well fitting, ventilated shoes, and change shoes and socks at least once daily. • Intended for use by normally healthy adults only. • Persons under 18 years of age or those with highly sensitive or allergic skin should use only as directed by a doctor. • Supervise children in the use of this product.

Other information: • FUNGICURE may be applied to exposed nail beds, to cuticles, around nail edges and under nail tips where reachable with its applicator brush. • This product is not intended to, nor will it, penetrate hard nail surfaces. • While not all finger and toe fungal infections are curable with OTC topical medications, if you see improvement within 4 weeks of use, you may continue to use FUNGICURE until satisfactory results are obtained. • You may report serious side effects to the phone number provided under Questions? below.

Inactive ingredienst: BHT, isopropyl alcohol, polyethylene glycol.

Questions? 1-800-792-2582

FUNGICURE.com

The active ingredient in FUNGICURE has been recognized to be safe and effective by an FDA Expert Advisory Panel, when used as directed.

Fungicure

LÍQUIDO ANTIFÚNGICO

Especialista en Hongos en Dedos de las Manos Y de los Pies

NADA MÁS POTENTE sin receta

Resultados visibles en an solo 4 semanas

Elimina 6 tipos de hongos

¿QUÉ ES UNA INFECCIÓN MICÓTICA EN LOS DEDOS DE LAS MANOS Y DE LOS PIES? Las infecciones tópicas de hongos comunes en los dedos de las manos y de los pies son causadas por una variedad de hongos; organismos reales vivos (miembros de la familia de la levadura y el moho) que prosperan en condiciones oscuras y húmedas. Usando pequeñas hendiduras en la superficie de la piel, estos organismos pueden causar infección por el contacto con superficies infectadas, animales o personas. Una vez que empieza la infección, puede ocurrir una propagación. Por ejemplo, los dedos infectados de las manos y de los pies pueden infectar a otros dedos. Aunque dichas infecciones a menudo se desarrollan lentamente, pueden ser difíciles de eliminar si no son tratadas de inmediato con una medicina antifúngica efectiva como FUNGICURE.

¿CÓMO SE SABE SI SE TIENE UNA INFECCIÓN TÓPICA DE HONGOS? Algunas infecciones tópicas micóticas pueden presentarse sobre la superficie de la piel como formaciones tipo anillo con centros claros; esto comúnmente se llama tiña. Los hongos de pie de atleta, cuando están en las áreas de los dedos de las manos y de los pies, se caracterizan a menudo por escamas en la piel, ardor, agrietamiento, comezón y otras molestias relacionadas. Cuando se infectan las uñas, pueden lucir opacas (blanco opaco), más gruesas, quebradizas, se rompen fácilmente y en algunos casos, descoloridas (verdosas o cafés).

COMPRENSIÓN Y TRATAMIENTO DE UNA INFECCIÓN EN EL ÁREA DE LAS UÑAS:

Las infecciones micóticas del área de las uñas a menudo son causadas por los mismos hongos que causan el pie de atleta y las infecciones de tiña en otros lugares del cuerpo. Estos hongos pueden infectar el área completa alrededor de las uñas incluyendo las cutículas, los lechos ungueales y hasta las mismas uñas. Cuando las uñas de los dedos de las manos o de los pies infectadas están intactas, los tratamientos antifúngicos tópicos de venta libre (OTC) podrían no ser capaces de penetrar en la uña y eliminar el hongo; por esto es que todos los tratamientos tópicos de venta libre (OTC) deben indicar que no son efectivos en las uñas. Sin embargo, en ocasiones de infecciones avanzadas, las uñas a menudo no están intactas; el dedo puede ya no tener la uña, las uñas pueden estar abiertas o levantadas, exponiendo el lecho ungueal infectado. En estos casos, el Líquido antifúngico FUNGICURE, con su potente fórmula antifúngica, puede alcanzar y eliminar los hongos del lecho ungueal a través de una aplicación directa o de una acción capilar relacionada. FUNGICURE cura la infección, permitiendo el nuevo crecimiento natural del tejido de aspecto saludable.

NOTA: Las infecciones micóticas que están aisladas dentro de una uña intacta o incrustadas dentro de la misma uña pueden requerir la consulta con un médico para recibir el tratamiento adecuado.

CÓMO FUNCIONA EL LÍQUIDO FUNGICURE:

El Líquido FUNGICURE de MÁXIMA CONCENTRACIÓN contiene tolnaftato, ingrediente antifúngico ampliamente reconocido que se ha comprobado efectivo contra 6 tipos de hongos tales como E. floccosum, T. mentagrophytes, M. canis, M. gypseum, T. tonsurans y T. rubrum.

Si se aplica según las instrucciones, FUNGICURE líquido actúa de inmediato para atacar, destruir y evitar la propagación de la infección inhibiendo el crecimiento y la reproducción de las células micóticas.

ACCIÓN INMEDIATA Y TRATAMIENTO ADECUADO:

Es importante tratar a tiempo las infecciones micóticas. Si sospecha que puede tener una infección micótica, consulte con su médico de inmediato para recibir la asesoría y el diagnóstico adecuados. Tal vez quiera mostrarle el FUNGICURE Líquido y conversar sobre su uso. Para obtener mejores resultados, una vez que se inicia el tratamiento con FUNGICURE Líquido, es importante seguir cuidadosamente las instrucciones de tratamiento en el empaque hasta que haya logrado resultados satisfactorios o hasta recibir más recomendaciones de parte de su médico.

NOTA: Puede esperarse una mejora notable en menos de 4 semanas en el caso de la mayoría de los hongos de tiña y pie de atleta. Consulte con su médico para recibir recomendaciones si no es evidente una mejora notable después de este tiempo o si la condición persiste o empeora.

Ingrediente activo: Tolnaftato al 1 %

Usos: Para curar la mayoría de los casos de: • tiña (tinea corporis) • pie de atleta (tinea pedis). Para aliviar: • comezón • descamación • agrietamiento ardor • enrojecimiento • dolor • irritación • incomodidades que pueden acompañar a estas condiciones. El uso diario ayuda a prevenir el pie de atleta en la mayoría los casos.

Advertencias:

Para uso externo solamente.

Consulte con su médico antes de usarlo en niños menores de 2 años de edad.

Cuando use este producto evite el contacto con los ojos.

Descontinúe el uso y consulte a un médico si • ocurre irritación • no hay mejoría en menos de 4 semanas.

Manténgalo fuera del alcance de los niños. Si es ingerido, obtenga asistencia médica o póngase en contacto de inmediato con un centro de control de envenenamiento.

Instrucciones: • Lea todas las instrucciones y advertencias en el empaque antes del uso. • Úselo solo según las instrucciones. • Limpie el área afectada con jabón y agua tibia, y séquela completamente. • Aplique una capa fina de FUNGICURE Líquido sobre el área afectada dos veces por día (en la mañana y en la noche) o según lo indique el médico. • Para prevenir el pie de atleta, lávese los pies y séquelos completamente. Aplique una capa fina del producto en los pies una o dos veces por día (mañana y/o noche). • Este producto no es efectivo sobre el cuero cabelludo o las uñas. • Contra la tiña y el pie de atleta, usar todos los días por 4 semanas. Si la condición persiste, consulte a su médico. • Para el tratamiento del pie de atleta, ponga atención especial a los espacios entre los dedos de los pies, utilice zapatos con ventilación que le queden bien, y cámbiese los zapatos y las medias por lo menos una vez por día. • Diseñado para usarlo en adultos normalmente saludables. • Las personas menores de 18 años de edad o aquellas con piel alérgica o altamente sensible deben usarlo solo según las instrucciones del médico. Supervise a los niños en el uso de este product.

Otra información: • FUNGICURE se puede aplicar a los lechos ungueales expuestos, las cuticulas, alrededor de los bordes de la uña y debajo de las puntas de las uñas que se puedan alcanzar con el cepillo aplicador. • Este producto no está previsto para las superficies duras de las uñas ni logrará penetrarlas. Aunque no todas las infecciones micóticas de los dedos de la mano y de los pies son curables con medicamentos tópicos de venta libre, si nota una mejoría en menos de 4 semanas de uso, puede continuar utilizando FUNGICURE hasta que obtenga resultados satisfactorios. • Puede reportar efectos secundarios serios al número telefónico provisto en ¿Preguntas? que aparece a continuación.

Ingrediente inactivo: BHT, alcohol isopropílico, polietilenglicol.

¿Preguntas? 1-800-792-2582

FUNGICURE.com

El ingrediente activo en FUNGICURE ha sido reconocido como seguro y efectivo por un Panel consultivo de expertos de la FDA, cuando se usa según las instrucciones.